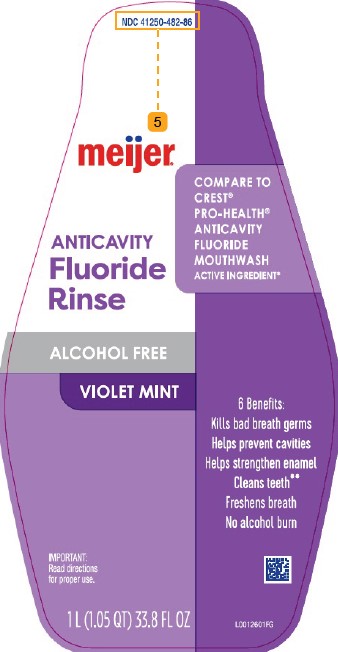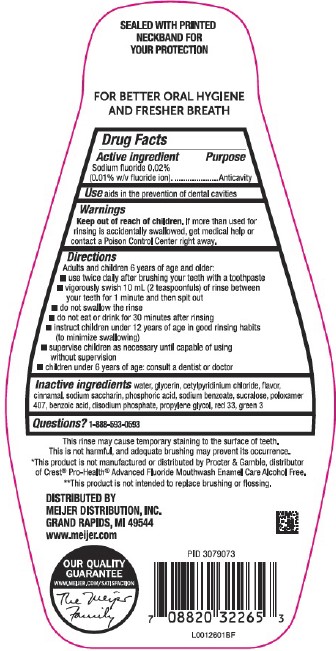 DRUG LABEL: Alcohol-Free Anticavity
NDC: 41250-482 | Form: LIQUID
Manufacturer: Meijer, Inc.
Category: otc | Type: HUMAN OTC DRUG LABEL
Date: 20260219

ACTIVE INGREDIENTS: SODIUM FLUORIDE 0.1 mg/1 mL
INACTIVE INGREDIENTS: WATER; GLYCERIN; CETYLPYRIDINIUM CHLORIDE; CINNAMALDEHYDE; SACCHARIN SODIUM; PHOSPHORIC ACID; SODIUM BENZOATE; SUCRALOSE; POLOXAMER 407; BENZOIC ACID; SODIUM PHOSPHATE, DIBASIC, ANHYDROUS; PROPYLENE GLYCOL; D&C RED NO. 33; FD&C GREEN NO. 3

Meijer 482.002/482AC
Alcohol Free Fluoride Violet Mint Mouthwash

Tamper Evident Statement

SEALED WITH PRINTED NECKBAND FOR YOUR PROTECTION

Claim

FOR BETTER ORAL HYGIENE AND FRESHER BREATH

Active ingredient

Sodium fluoride 0.02% (0.01 w/v fluoride ion)

Purpose

Anticavity

Use

aids in the preveiontion of dental cavities

Warnings

for this product

Keep out of reach of children.

If more than used for rinsing is accidentally swallowed, get medical help or contact a Poison Control Center right away.

Directions

Adults and children 6 years of age and older:

- use twice daily after brushing your teeth with a toothpaste
- vigorously swish 10 mL (2 teaspoonfuls) of rinse between your teeth for 1 minute and then spit out
- do not swallow the rinse
- do not eat or drink for 30 minutes after rinsing
- instruct children under 12 years of age in good rinsing habits (to minimize swallowing)
- supervise children as necessary until capable of using without supervision
- children under 6 years of age: consult a dentist or doctor

Inactive ingredients

water, glycerin, cetylpyridinium chloride, flavor, cinnamal, sodium saccharin, phosphoric acid, sodium benzoate, sucralose, poloxamer 407, benzoic acid, disodium phosphate, propylene glycol, red 33, green 3

Questions?

1-888-593-0593

Warnings for CPC Containing Products

This rinse may cause temporary staining to the surface of teeth.

This is not harmful, and adequate brushing may prevent its occurrence.

Disclaimers

*Ths product is not manufactured or distributed by Procter & Gamble, distributor of Crest® Pro-Health® Advanced Fluoride Mouthwash Enamel Care Alcohol Free.

**This product is not intended to replace brushing or flossing.

Adverse Reaction

DISTRIBUTED BY

MEIJER DISTRIBUTION, INC.

2929 WALKER AVE NW

GRAND RAPIDS, MI 49544

www.meijer.com

OUR QUALITY GUARANTEE

WWW.MEIJER.COM/SATISFACTION

The Meijer Family

Principal display panel

NDC 41250-482-86

meijer®

*COMPARE TO CREST® PRO-HEALTH®ANTICAVITY FLUORIDE MOUTHWASH ACTIVE INGREDIENT*

ANTICAVITY

Fluoride Rinse

ALCOHOL FREE

VIOLET MINT

6 Benefits:

Kills bad breath germs

Helps prevent cavities

Helps strengthen enamel

Cleans teeth**

Freshens breath

No alcohol burn

IMPORTANT: Read directions for proper use.

1 L (1.05 QT) 33.8 FL OZ